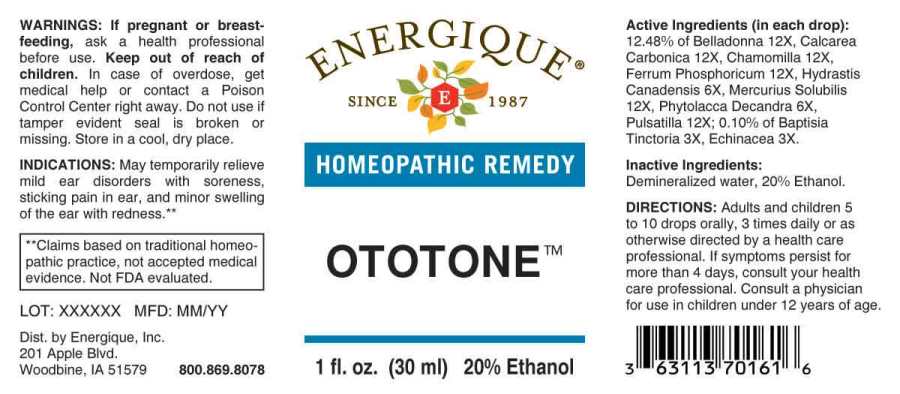 DRUG LABEL: Ototone
NDC: 44911-0467 | Form: LIQUID
Manufacturer: Energique, Inc.
Category: homeopathic | Type: HUMAN OTC DRUG LABEL
Date: 20241029

ACTIVE INGREDIENTS: BAPTISIA TINCTORIA ROOT 3 [hp_X]/1 mL; ECHINACEA ANGUSTIFOLIA WHOLE 3 [hp_X]/1 mL; GOLDENSEAL 6 [hp_X]/1 mL; PHYTOLACCA AMERICANA ROOT 6 [hp_X]/1 mL; ATROPA BELLADONNA 12 [hp_X]/1 mL; OYSTER SHELL CALCIUM CARBONATE, CRUDE 12 [hp_X]/1 mL; MATRICARIA CHAMOMILLA WHOLE 12 [hp_X]/1 mL; FERROSOFERRIC PHOSPHATE 12 [hp_X]/1 mL; MERCURIUS SOLUBILIS 12 [hp_X]/1 mL; PULSATILLA PRATENSIS WHOLE 12 [hp_X]/1 mL
INACTIVE INGREDIENTS: WATER; ALCOHOL

DRUG FACTS:

ACTIVE INGREDIENTS:

(in each drop): 12.48% of Belladonna 12X, Calcarea Carbonica 12X, Chamomilla 12X, Ferrum Phosphoricum 12X, Hydrastis Canadensis 6X, Mercurius Solubilis 12X, Phytolacca Decandra 6X, Pulsatilla (Pratensis) 12X; 0.10% of Baptisia Tinctoria 3X, Echinacea Angustifolia 3X.

INDICATIONS:

May temporarily relieve mild ear disorders with soreness, sticking pain in ear, and minor swelling of the ear with redness.**

**Claims based on traditional homeopathic practice, not accepted medical evidence. Not FDA evaluated.

WARNINGS:

If pregnant or breast-feeding, ask a health professional before use.

Keep out of reach of children. In case of overdose, get medical help or contact a Poison Control Center right away.

Do not use if tamper evident seal is broken or missing. Store in a cool, dry place.

Keep out of reach of children. In case of overdose, get medical help or contact a Poison Control Center right away.

DIRECTIONS:

Adults and children 5 to 10 drops orally, 3 times daily or as otherwise directed by a health care professional. If symptoms persist for more than 4 days, consult your health care professional. Consult a physician for use in children under 12 years of age.

INDICATIONS:

May temporarily relieve mild ear disorders with soreness, sticking pain in ear, and minor swelling of the ear with redness.**

**Claims based on traditional homeopathic practice, not accepted medical evidence. Not FDA evaluated.

INACTIVE INGREDIENTS:

Demineralized water, 20% Ethanol.

QUESTIONS:

Dist. by Energique, Inc.

201 Apple Blvd

Woodbine, IA 51579 800.869.8078

PACKAGE LABEL DISPLAY:

ENERGIQUE

SINCE 1987

HOMEOPATHIC REMEDY

OTOTONE

1 fl. oz. (30 ml)